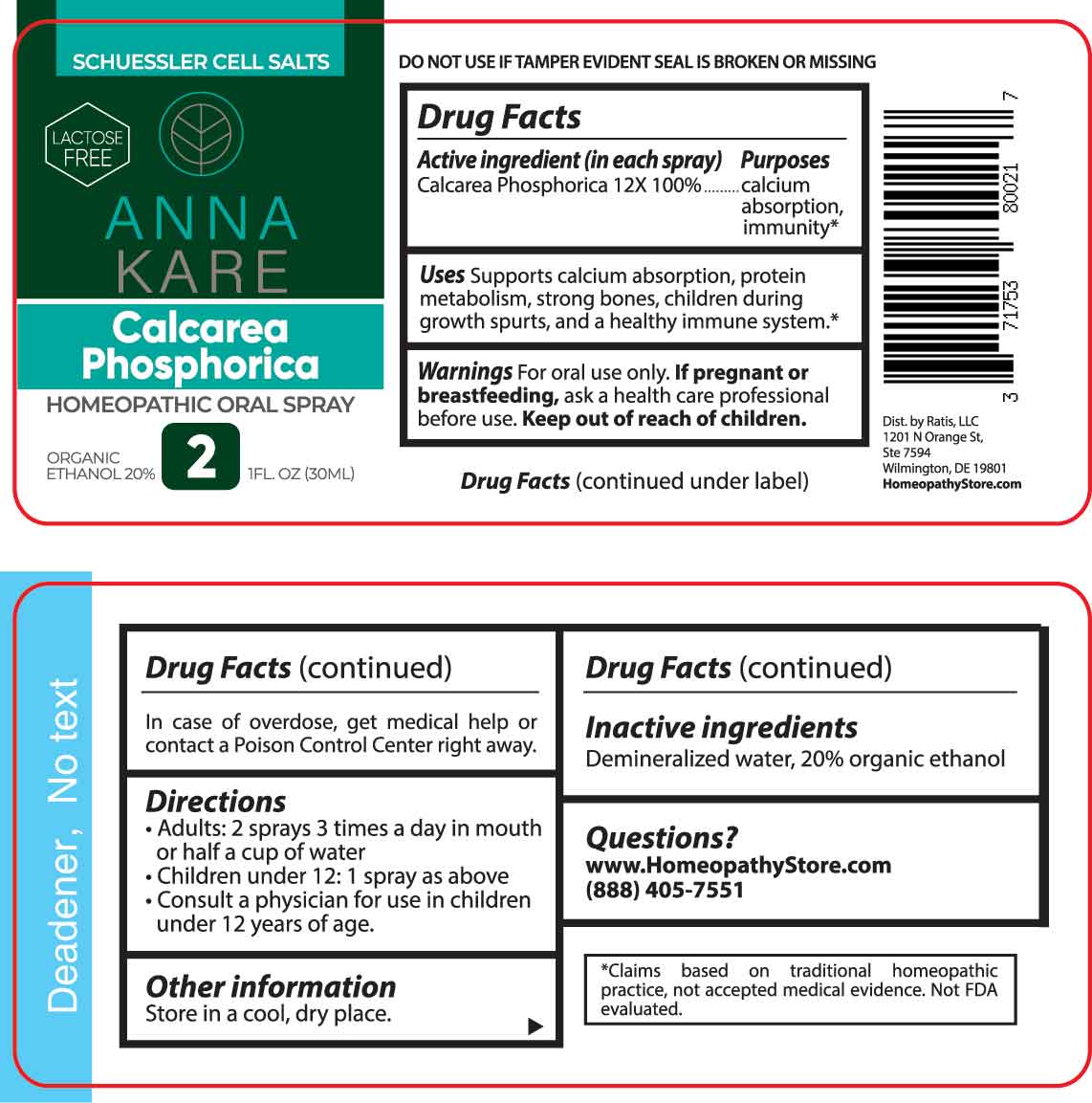 DRUG LABEL: Calcarea Phosphorica
NDC: 71753-8002 | Form: SPRAY
Manufacturer: Ratis, LLC
Category: homeopathic | Type: HUMAN OTC DRUG LABEL
Date: 20230713

ACTIVE INGREDIENTS: TRIBASIC CALCIUM PHOSPHATE 12 [hp_X]/1 mL
INACTIVE INGREDIENTS: WATER; ALCOHOL

DRUG FACTS:

ACTIVE INGREDIENT:

(in each spray) Calcarea Phosphorica 12X 100%.

PURPOSES:

Calcarea Phosphorica - calcium absorption, immunity*

USES:

Supports calcium absorption, protein metabolism, strong bones, children during growth spurts, and a healthy immune system.*

*Claims based on traditional homeopathic practice, not accepted medial evidence. Not FDA evaluated.

WARNINGS:

For oral use only.

If pregnant or breast-feeding, or if symptoms persist or worsen, ask a health care professional.

Keep out of reach of children. In case of overdose, get medical help or contact a Poison Control Center right away.

DO NOT USE IF TAMPER EVIDENT SEAL IS BROKEN OR MISSING

KEEP OUT OF REACH OF CHILDREN:

In case of overdose, get medical help or contact a Poison Control Center right away.

DIRECTIONS:

• Adults: 2 sprays 3 times a day in mouth or half a cup of water.

• Children under 12: 1 spray as above.

• Consult a physician for use in children under 12 years of age.

Store in a cool, dry place.

INACTIVE INGREDIENTS:

Demineralized water, 20% organic ethanol

QUESTIONS:

www.HomeopathyStore.com

(888) 405-7551

Dist. by Ratis, LLC

1201 N Orange St.

Ste 7594

Wilmington, DE 19801

PACKAGE LABEL DISPLAY:

SCHUESSLER CELL SALTS

LACTOSE FREE

ANNA

KARE

Calcarea

Phosphorica

HOMEOPATHIC ORAL SPRAY

1 FL. OZ (30ML)